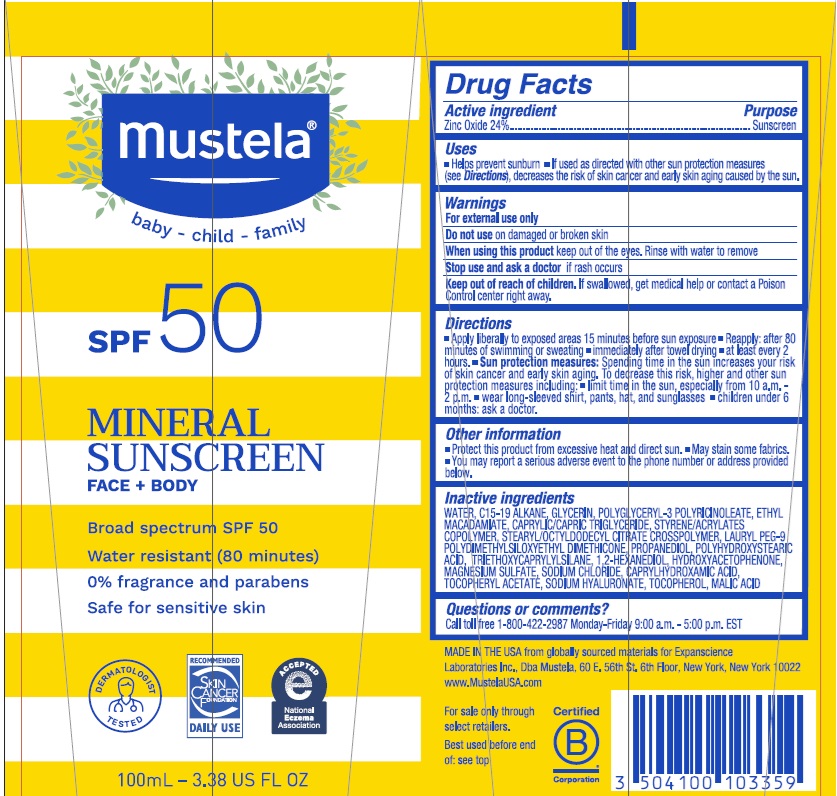 DRUG LABEL: MUSTELA MINERAL SUNSCREEN BROAD SPECTRUM SPF 50
NDC: 64768-2924 | Form: LOTION
Manufacturer: Expanscience Laboratories d/b/a Mustela
Category: otc | Type: HUMAN OTC DRUG LABEL
Date: 20250602

ACTIVE INGREDIENTS: ZINC OXIDE 240 mg/1 mL
INACTIVE INGREDIENTS: WATER; GLYCERIN; POLYGLYCERYL-3 RICINOLEATE; MEDIUM-CHAIN TRIGLYCERIDES; BUTYL METHACRYLATE/METHYL METHACRYLATE/METHACRYLIC ACID/STYRENE CROSSPOLYMER; PROPANEDIOL; 1,2-HEXANEDIOL; MAGNESIUM SULFATE, UNSPECIFIED FORM; SODIUM CHLORIDE; CAPRYLHYDROXAMIC ACID; HYALURONATE SODIUM; MALIC ACID; LAURYL PEG-9 POLYDIMETHYLSILOXYETHYL DIMETHICONE; C15-19 ALKANE; ETHYL MACADAMIATE; STEARYL/OCTYLDODECYL CITRATE CROSSPOLYMER; TRIETHOXYCAPRYLYLSILANE; POLYHYDROXYSTEARIC ACID (2300 MW); HYDROXYACETOPHENONE; .ALPHA.-TOCOPHEROL ACETATE; .ALPHA.-TOCOPHEROL, D-

MUSTELA MINERAL SUNSCREEN BROAD SPECTRUM SPF 50

Active Ingredient

Zinc Oxide 24%

Purpose

Sunscreen

Uses

- Helps prevent sunburn
- If used as directed wtih other sun protection measures (see Directions), decreases the risk of skin cancer and early skin aging caused by the sun.

Warnings

For external use only.

Do not use on damaged or broken skin.

When using this product keep out of the eyes. Rinse with water to remove.

Stop use and ask a doctor if rash occurs.

Keep out of reach of children. If swallowed, get medical help or contact a Poison Control center right away.

Directions

- Apply liberally to exposed areas 15 minutes before sun exposure.
- Reapply: after 80 minutes of swimming or sweating.
- immediately after towel drying.
- at least every 2 hours.
- Sun protection measures: Spending time in the sun increases your risk of skin cancer and early skin aging. To decrease this risk, regularly use a sunscreen with a broad spectrum SPF of 15 or higher and other sun protection measures including:
- limit time in the sun, expecially from 10 a.m. - 2 p.m.
- wear long-sleeved shirt, pants, hat and sunglasses
- children under 6 months: ask a doctor

Other information

- Protect this product from excessive heat and direct sun.
- May stain some fabrics.
- You may report a serious adverse event to the phone number or address provided below.

Inactive ingredients

WATER, C15-19 ALKANE, GLYCERIN, POLYGLYCERYL-3 POLYRICINOLEATE, ETHYL MACADAMIATE, CAPRYLIC/CAPRIC TRIGLYCERIDE, STYRENE/ACRYLATES COPOLYMER, STEARYL/OCTYLDODECYL CITRATE CROSSPOLYMER, LAURYL PEG-9 POLYDIMETHYLSILOXYETHYL DIMETHICONE, PROPANEDIOL, POLYHYDROXYSTEARIC ACID, TRIETHOXYCAPRYLYLSILANE, 1,2-HEXANEDIOL, HYDROXYACETOPHENONE, MAGNESIUM SULFATE, SODIUM CHLORIDE, CAPRYLHYDROXAMIC ACID, TOCOPHERYL ACETATE, SODIUM HYALURONATE, TOCOPHEROL, MALIC ACID

Questions or comments?

Call toll free 1-800-422-2987 Monday-Friday 9:00am - 5:00pm EST

Company Information

MADE IN THE USA from globally sourced materials for Expanscience Laboratories Inc., Dba Mustela, 60 E. 56th St. 6th Floor, New York, New York 10022

www.MustelaUSA.com